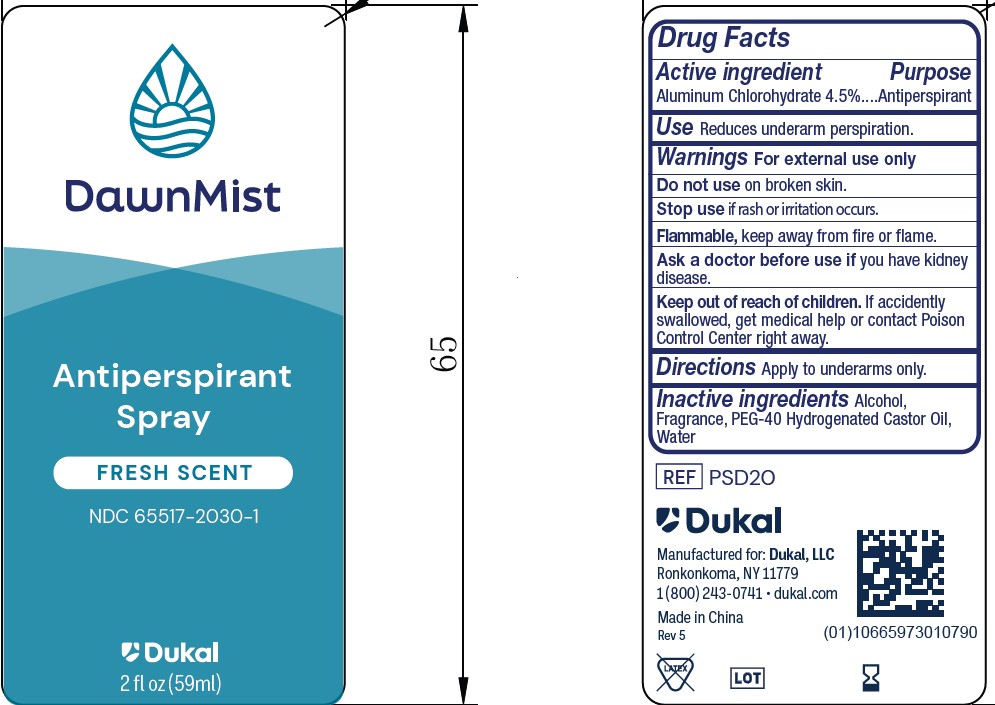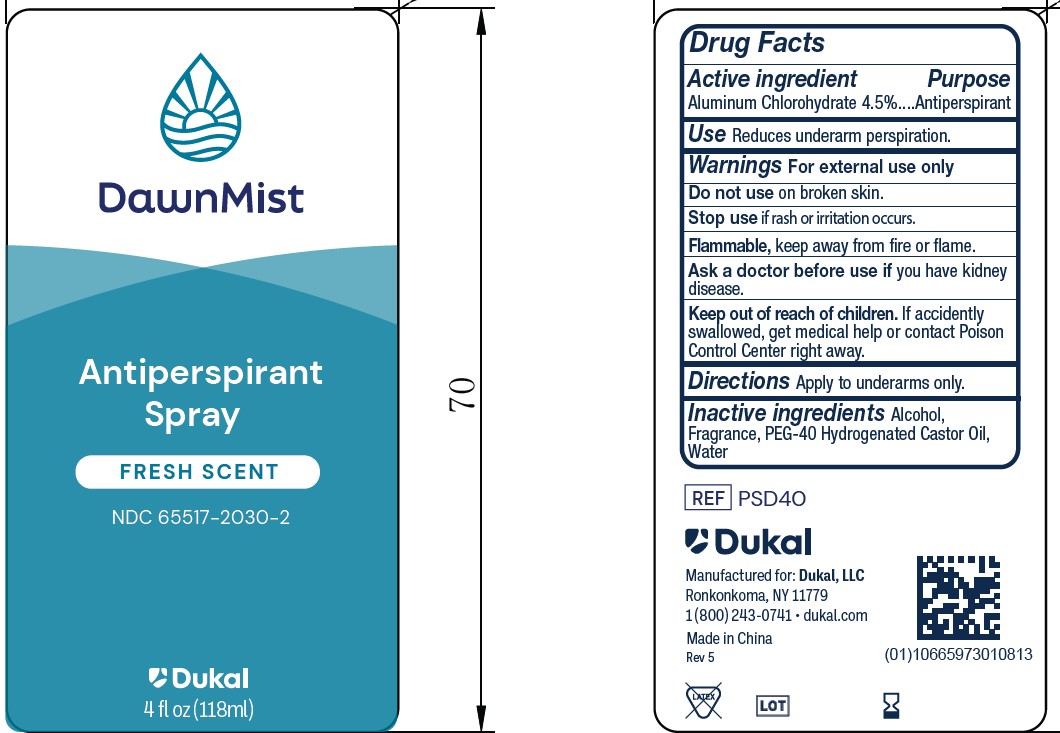 DRUG LABEL: DawnMist Antiperspirant
NDC: 65517-2030 | Form: LIQUID
Manufacturer: Dukal LLC
Category: otc | Type: HUMAN OTC DRUG LABEL
Date: 20241219

ACTIVE INGREDIENTS: ALUMINUM CHLOROHYDRATE 45 mg/1 mL
INACTIVE INGREDIENTS: POLYOXYL 40 HYDROGENATED CASTOR OIL; WATER; ALCOHOL 95%

DawnMist Antiperspirant Spray 4.5%

Active Ingredient

Aluminum Chlorohydrate 4.5%

Purpose

Antiperspirant

Use

Reduces underarm perspiration

Warnings

For external use only.

Flammable, keep away from fire or flame.

Do not use on broken skin

Stop use

Stop use if rash or irritation occurs.

Ask a doctor before use if you have kidney disease.

Keep out of reach of children. If accidently swallowed, get medical help or contact Poison Control Center right away.

Directions

Apply to underarms only.

Inactive ingredients

Alcohol, Fragrance, PEG-40 Hydrogenated Castor Oil, Water

PACKAGE LABEL

DawnMist

Antiperspirant

Spray

Fresh Scent

NDC 65517-2030-1

Dukal

2FL.OZ. (59ml)

PACKAGE LABEL

NDC 65517-2030-2

DawnMist

Personal Care

Antiperspirant

Spray

Fresh Scent

4FL.OZ. (118ml)